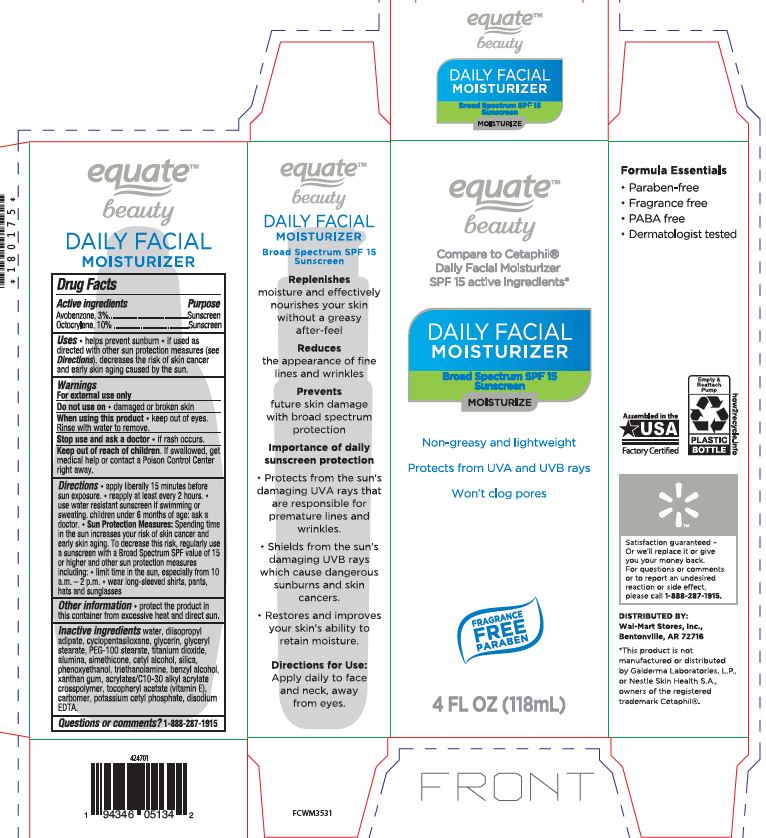 DRUG LABEL: Daily Facial Moisturizer SPF 15


NDC: 79903-203 | Form: LOTION
Manufacturer: Walmart
Category: otc | Type: HUMAN OTC DRUG LABEL
Date: 20240306

ACTIVE INGREDIENTS: AVOBENZONE 3 g/100 mL; OCTOCRYLENE 10 g/100 mL
INACTIVE INGREDIENTS: WATER; XANTHAN GUM; GLYCERIN; EDETATE DISODIUM ANHYDROUS; CARBOMER COPOLYMER TYPE B (ALLYL PENTAERYTHRITOL CROSSLINKED); CARBOMER 934; DIISOPROPYL ADIPATE; TITANIUM DIOXIDE; ALUMINUM OXIDE; SILICON DIOXIDE; GLYCERYL STEARATE CITRATE; PEG-100 STEARATE; CYCLOMETHICONE 5; .ALPHA.-TOCOPHEROL ACETATE; PHENOXYETHANOL; CETYL ALCOHOL; BENZYL ALCOHOL; POTASSIUM CETYL PHOSPHATE

PLSF-1818 Daily Facial Moisturizer SPF 15

Active ingredients Purpose

Avonenzone 3% Sunscreen

Octocrylene 10% Sunscreen

Uses

•helps prevent sunburn• If used as directed with other sun protection measures (see Oirections),decreases the risk of skin cancer and early skin aging caused by the sun.

Do not use on

• damaged or broken skin.

When using this product

•keep out of eyes. Rinse with waterto remove.

Stop use and ask a doctor

• if rash occurs.

Directions:

• apply liberal 15 minutes before sun exposure• reapply at least every 2 hours •use a water resistant sunscreen if swimmingor sweating•children under 6 months of age: ask a doctor• Sun Protection Measures:Spending time in the sun increase your risk of skin cancer and early skin aging. To decrease this risk. regularly usea sunscreen wrtha Broad Spectrum SPF value of15 or higher and other suncrin protection measures including:
• limrt time in the sun, especial from 10a.m. -2 p.rn.•wear long-sleeve shorts , pants, hats and sunglasses

Inactive Ingredients

Water
Xanthan Gum
Glycerin
Disodium EDTA
Acrylates/C10-30 Alkyl Acrylate Crosspolymer
Carbomer
Diisopropyl Adipate
Titanium Dioxide, Alumina, Simethicone
Glyceryl Stearate, PEG-100 Stearate
Cyclopentasiloxane
Tocopheryl Acetate
Phenoxyethanol
Cetyl Alcohol
Benzyl Alcohol
Potassium Cetyl Phosphate